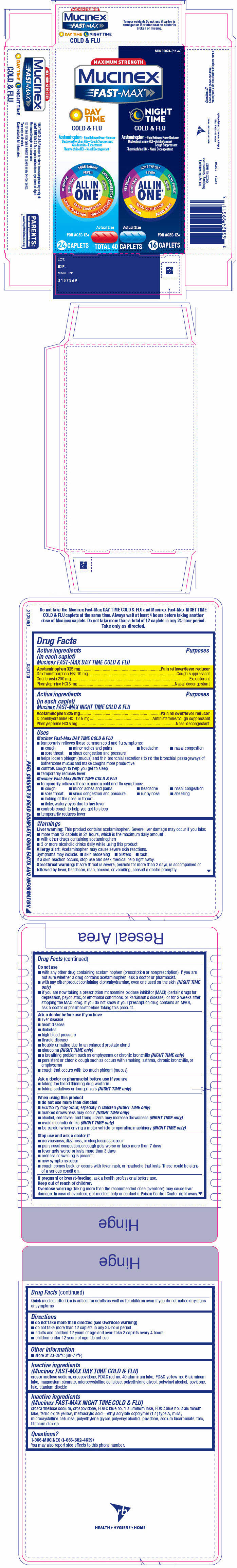 DRUG LABEL: Maximum Strength Mucinex Fast-Max Day Time Cold and Flu and Night Time Cold and Flu
NDC: 63824-511 | Form: KIT | Route: ORAL
Manufacturer: RB Health (US) LLC
Category: otc | Type: HUMAN OTC DRUG LABEL
Date: 20201027

ACTIVE INGREDIENTS: Acetaminophen 325 mg/1 1; Guaifenesin 200 mg/1 1; Dextromethorphan Hydrobromide 10 mg/1 1; Phenylephrine Hydrochloride 5 mg/1 1; Acetaminophen 325 mg/1 1; Diphenhydramine Hydrochloride 12.5 mg/1 1; Phenylephrine Hydrochloride 5 mg/1 1
INACTIVE INGREDIENTS: croscarmellose sodium; CROSPOVIDONE; FD&C red no. 40; FD&C yellow no. 6; ALUMINUM OXIDE; Magnesium stearate; microcrystalline cellulose; POLYETHYLENE GLYCOL, UNSPECIFIED; POLYVINYL ALCOHOL, UNSPECIFIED; POVIDONE, UNSPECIFIED; talc; titanium dioxide; croscarmellose sodium; CROSPOVIDONE; FD&C blue no. 1; FD&C blue no. 2; ALUMINUM OXIDE; ferric oxide yellow; METHACRYLIC ACID - ETHYL ACRYLATE COPOLYMER (1:1) TYPE A; mica; microcrystalline cellulose; POLYETHYLENE GLYCOL, UNSPECIFIED; POLYVINYL ALCOHOL, UNSPECIFIED; POVIDONE, UNSPECIFIED; sodium bicarbonate; talc; titanium dioxide

Maximum Strength Mucinex® Fast-Max® Day Time Cold & Flu and Night Time Cold & Flu

Drug Facts

ACTIVE INGREDIENT

PURPOSE

Active ingredients (in each caplet) | Purposes
Mucinex FAST-MAX DAY TIME COLD & FLU
Acetaminophen 325 mg | Pain reliever/fever reducer
Dextromethorphan HBr 10mg | Cough suppressant
Guaifenesin 200 mg | Expectorant
Phenylephrine HCl 5 mg | Nasal decongestant

Active ingredients (in each caplet) | Purposes
Mucinex FAST-MAX NIGHT TIME COLD & FLU
Acetaminophen 325 mg | Pain reliever/fever reducer
Diphenhydramine HCl 12.5 mg | Antihistamine/cough suppressant
Phenylephrine HCl 5 mg | Nasal decongestant

Uses

Mucinex Fast-Max DAY TIME COLD & FLU

- temporarily relieves these common cold and flu symptoms:
  - cough
  - minor aches and pains
  - headache
  - nasal congestion
  - sore throat
  - sinus congestion and pressure
- helps loosen phlegm (mucus) and thin bronchial secretions to rid the bronchial passageways of bothersome mucus and make coughs more productive
- controls cough to help you get to sleep
- temporarily reduces fever

Mucinex Fast-Max NIGHT TIME COLD & FLU

- temporarily relieves these common cold and flu symptoms:
  - cough
  - minor aches and pains
  - headache
  - nasal congestion
  - sore throat
  - sinus congestion and pressure
  - runny nose
  - sneezing
  - itching of the nose or throat
  - itchy, watery eyes due to hay fever
- controls cough to help you get to sleep
- temporarily reduces fever

Warnings

Liver warning

This product contains acetaminophen. Severe liver damage may occur if you take:

- more than 12 caplets in 24 hours, which is the maximum daily amount
- with other drugs containing acetaminophen
- 3 or more alcoholic drinks daily while using this product

Allergy alert

Acetaminophen may cause severe skin reactions. Symptoms may include:

- skin reddening
- blisters
- rash

If a skin reaction occurs, stop use and seek medical help right away.

Sore throat warning

If sore throat is severe, persists for more than 2 days, is accompanied or followed by fever, headache, rash, nausea, or vomiting, consult a doctor promptly.

Do not use

- with any other drug containing acetaminophen (prescription or nonprescription). If you are not sure whether a drug contains acetaminophen, ask a doctor or pharmacist.
- with any other product containing diphenhydramine, even one used on the skin (NIGHT TIME only)
- if you are now taking a prescription monoamine oxidase inhibitor (MAOI) (certain drugs for depression, psychiatric, or emotional conditions, or Parkinson's disease), or for 2 weeks after stopping the MAOI drug. If you do not know if your prescription drug contains an MAOI, ask a doctor or pharmacist before taking this product.

Ask a doctor before use if you have

- liver disease
- heart disease
- diabetes
- high blood pressure
- thyroid disease
- trouble urinating due to an enlarged prostate gland
- glaucoma (NIGHT TIME only)
- a breathing problem such as emphysema or chronic bronchitis (NIGHT TIME only)
- persistent or chronic cough such as occurs with smoking, asthma, chronic bronchitis, or emphysema
- cough that occurs with too much phlegm (mucus)

Ask a doctor or pharmacist before use if you are

- taking the blood thinning drug warfarin
- taking sedatives or tranquilizers (NIGHT TIME only)

When using this product

- do not use more than directed
- excitability may occur, especially in children (NIGHT TIME only)
- marked drowsiness may occur (NIGHT TIME only)
- alcohol, sedatives, and tranquilizers may increase drowsiness (NIGHT TIME only)
- avoid alcoholic drinks (NIGHT TIME only)
- be careful when driving a motor vehicle or operating machinery (NIGHT TIME only)

Stop use and ask a doctor if

- nervousness, dizziness, or sleeplessness occur
- pain, nasal congestion, or cough gets worse or lasts more than 7 days
- fever gets worse or lasts more than 3 days
- redness or swelling is present
- new symptoms occur
- cough comes back, or occurs with fever, rash, or headache that lasts. These could be signs of a serious condition.

PREGNANCY OR BREAST FEEDING

If pregnant or breast-feeding, ask a health professional before use.

Keep out of reach of children.

Overdose warning

Taking more than the recommended dose (overdose) may cause liver damage. In case of overdose, get medical help or contact a Poison Control Center right away. Quick medical attention is critical for adults as well as for children even if you do not notice any signs or symptoms.

Directions

- do not take more than directed (see Overdose warning)
- do not take more than 12 caplets in any 24-hour period
- adults and children 12 years of age and over: take 2 caplets every 4 hours
- children under 12 years of age: do not use

Other information

- store at 20-25°C (68-77°F)

Inactive ingredients

(Mucinex FAST-MAX DAY TIME COLD & FLU)

croscarmellose sodium, crospovidone, FD&C red no. 40 aluminum lake, FD&C yellow no. 6 aluminum lake, magnesium stearate, microcrystalline cellulose, polyethylene glycol, polyvinyl alcohol, povidone, talc, titanium dioxide

Inactive ingredients

(Mucinex FAST-MAX NIGHT TIME COLD & FLU)

croscarmellose sodium, crospovidone, FD&C blue no. 1 aluminum lake, FD&C blue no. 2 aluminum lake, ferric oxide yellow, methacrylic acid – ethyl acrylate copolymer (1:1) type A, mica, microcrystalline cellulose, polyethylene glycol, polyvinyl alcohol, povidone, sodium bicarbonate, talc, titanium dioxide

Dist. by: RB Health (US)
Parsippany, NJ 07054-0224

PRINCIPAL DISPLAY PANEL - Kit Carton

NDC 63824-511-40

MAXIMUM STRENGTH
Mucinex®
FAST-MAX®

DAY
TIME
COLD & FLU

Acetaminophen – Pain Reliever/Fever Reducer
Dextromethorphan HBr – Cough Suppressant
Guaifenesin – Expectorant
Phenylephrine HCl – Nasal Decongestant

HEADACHE
BODY PAIN
SORE THROAT
FEVER
CHEST CONGESTION
COUGH
ALL IN
ONE*
NASAL CONGESTION
SINUS CONGESTION
SINUS PRESSURE

Actual Size

FOR AGES 12+

24 CAPLETS

NIGHT
TIME
COLD & FLU

Acetaminophen – Pain Reliever/Fever Reducer
Diphenhydramine HCl – Antihistamine/
Cough Suppressant
Phenylephrine HCl – Nasal Decongestant

HEADACHE
BODY PAIN
SORE THROAT
FEVER
ITCHY THROAT
COUGH
ALL IN
ONE*
NASAL CONGESTION
SNEEZING
RUNNY NOSE

Actual Size

FOR AGES 12+

16 CAPLETS

TOTAL 40 CAPLETS